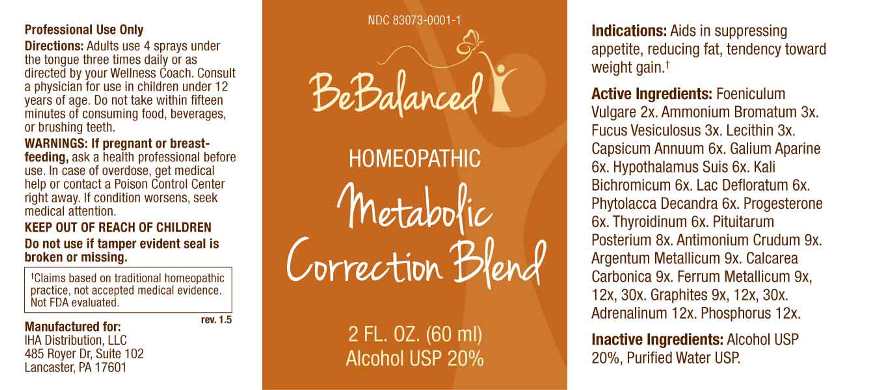 DRUG LABEL: Metabolic Correction Blend
NDC: 83073-0001 | Form: SPRAY
Manufacturer: IHA Distribution, LLC
Category: homeopathic | Type: HUMAN OTC DRUG LABEL
Date: 20230321

ACTIVE INGREDIENTS: FOENICULUM VULGARE FRUIT 2 [hp_X]/1 mL; AMMONIUM BROMIDE 3 [hp_X]/1 mL; FUCUS VESICULOSUS 3 [hp_X]/1 mL; EGG PHOSPHOLIPIDS 3 [hp_X]/1 mL; CAPSICUM 6 [hp_X]/1 mL; GALIUM APARINE WHOLE 6 [hp_X]/1 mL; SUS SCROFA PITUITARY GLAND 6 [hp_X]/1 mL; POTASSIUM DICHROMATE 6 [hp_X]/1 mL; SKIM MILK 6 [hp_X]/1 mL; PHYTOLACCA AMERICANA ROOT 6 [hp_X]/1 mL; PROGESTERONE 6 [hp_X]/1 mL; THYROID, BOVINE 6 [hp_X]/1 mL; BOS TAURUS PITUITARY GLAND, POSTERIOR 8 [hp_X]/1 mL; ANTIMONY TRISULFIDE 9 [hp_X]/1 mL; SILVER 9 [hp_X]/1 mL; OYSTER SHELL CALCIUM CARBONATE, CRUDE 9 [hp_X]/1 mL; IRON 9 [hp_X]/1 mL; GRAPHITE 9 [hp_X]/1 mL; EPINEPHRINE 12 [hp_X]/1 mL; PHOSPHORUS 12 [hp_X]/1 mL
INACTIVE INGREDIENTS: WATER; ALCOHOL

DRUG FACTS:

ACTIVE INGREDIENTS:

Foeniculum Vulgare 2X, Ammonium Bromatum 3X, Fucus Vesiculosus 3X, Lecithin 3X, Capsicum Annuum 6X, Galium Aparine 6X, Hypothalamus Suis 6X, Kali Bichromicum 6X, Lac Defloratum 6X, Phytolacca Decandra 6X, Progesterone 6X, Thyroidinum 6X, Pituitarum Posterium 8X, Antimonium Crudum 9X, Argentum Metallicum 9X, Calcarea Carbonica 9X, Ferrum Metallicum 9X, 12X, 30X, Graphites 9X, 12X, 30X, Adrenalinum 12X, Phosphorus 12X.

PURPOSE:

Aids in suppressing appetite, reducing fat, tendency toward weight gain.†

†Claims based on traditional homeopathic practice, not accepted medical evidence. Not FDA evaluated.

WARNINGS:

Professional Use Only

If pregnant or breast-feeding, ask a health professional before use.

In case of overdose, get medical help or contact a Poison Control Center right away.

If condition worsens, seek medical attention.

KEEP OUT OF REACH OF CHILDREN

Do not use if tamper evident seal is broken or missing.

KEEP OUT OF REACH OF CHILDREN:

In case of overdose, get medical help or contact a Poison Control Center right away.

DIRECTIONS:

Adults use 4 sprays under the tongue three times daily or as directed by your Wellness Coach. Consult a physician for use in children under 12 years of age. Do not take within fifteen minutes of consuming food, beverages, or brushing teeth.

INDICATIONS:

Aids in suppressing appetite, reducing fat, tendency toward weight gain.†

†Claims based on traditional homeopathic practice, not accepted medical evidence. Not FDA evaluated.

INACTIVE INGREDIENTS:

Alcohol USP 20%, Purified Water USP.

QUESTIONS:

Manufactured for:

IHA Distribution, LLC

485 Royer Dr, Suite 102

Lancaster, PA 17601

PACKAGE LABEL DISPLAY:

NDC 83073-0001-1

BeBalanced

HOMEOPATHIC

Metabolic

Correction Blend

2FL. OZ. (60 ml)